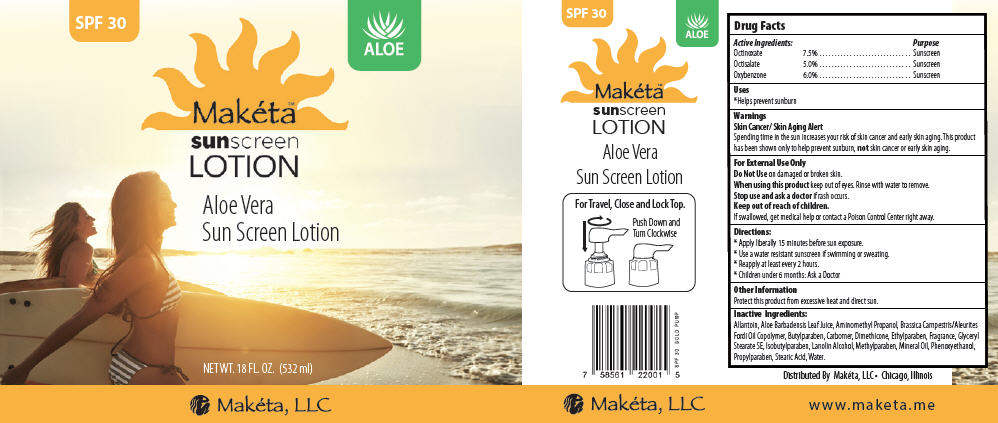 DRUG LABEL: Maketa Sunscreen with Aloe Vera SPF 30
NDC: 72102-047 | Form: LOTION
Manufacturer: Makéta™ Sunscreen Lotion with Aloe Vera SPF 30
Category: otc | Type: HUMAN OTC DRUG LABEL
Date: 20200109

ACTIVE INGREDIENTS: Octinoxate 75 mg/1 mL; Octisalate 50 mg/1 mL; Oxybenzone 60 mg/1 mL
INACTIVE INGREDIENTS: Water; Allantoin; Carbomer Homopolymer Type B (Allyl Sucrose Crosslinked); Gulose, L-; Mineral Oil; Hexamethyldisiloxane; Aminomethylpropanol; Stearic Acid; Aloe vera leaf; Phenoxyethanol; Glyceryl Stearate SE; Cetostearyl alcohol; Polysorbate 60

Makéta™ Sunscreen Lotion with Aloe Vera SPF 30

Drug Facts

ACTIVE INGREDIENT

Active Ingredients: |  | Purpose
Octinoxate | 7.5% | Sunscreen
Octisalate | 5.0% | Sunscreen
Oxybenzone | 6.0% | Sunscreen

Uses

- Helps prevent sunburn

Warnings

Skin Cancer/ Skin Aging Alert

Spending time in the sun increases your risk of skin cancer and early skin aging. This product has been shown only to help prevent sunburn, not skin cancer or early skin aging.

Do Not Use on damaged or broken skin.

When using this product keep out of eyes. Rinse with water to remove.

Stop use and ask a doctor if rash occurs.

Keep out of reach of children.

If swallowed, get medical help or contact a Poison Control Center right away.

Directions

- Apply liberally 15 minutes before sun exposure.
- Use a water resistant sunscreen if swimming or sweating.
- Reapply at least every 2 hours.
- Children under 6 months: Ask a Doctor

Other Information

Protect this product from excessive heat and direct sun.

Inactive Ingredients

Allantoin, Aloe Barbadensis Leaf Juice, Aminomethyl Propanol, Brassica Campestris/Aleurites Fordi Oil Copolymer, Butylparaben, Carbomer, Dimethicone, Ethylparaben, Fragrance, Glyceryl Stearate SE, Isobutylparaben, Lanolin Alcohol, Methylparaben, Mineral Oil, Phenoxyethanol, Propylparaben, Stearic Acid, Water.

Distributed By Makéta, LLC • Chicago, Illinois

PRINCIPAL DISPLAY PANEL - 532 ml Bottle Label

SPF 30

ALOE

Makéta™
sunscreen
LOTION

Aloe Vera
Sun Screen Lotion

NET WT. 18 FL. OZ. (532 ml)

Makéta, LLC